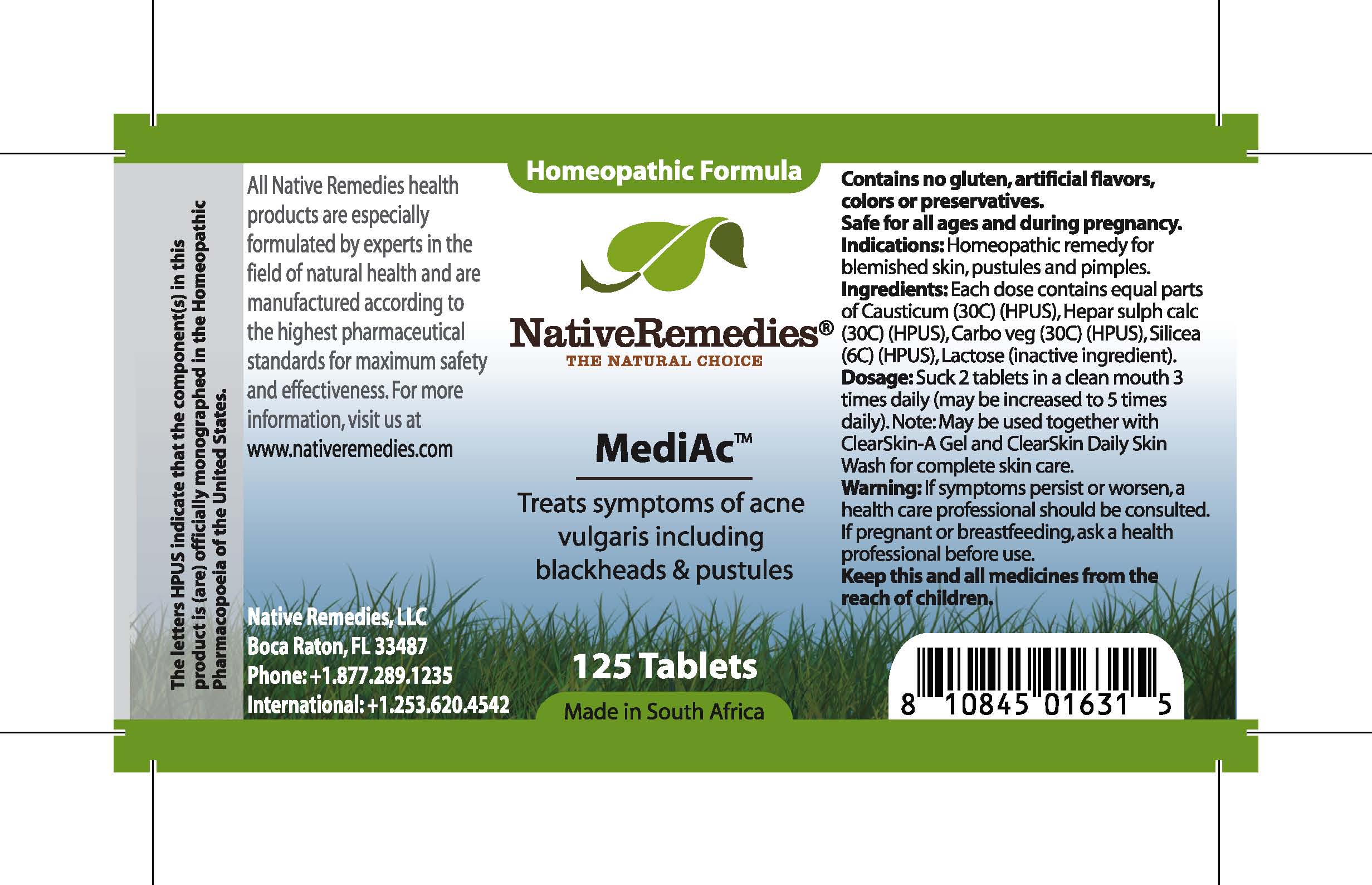 DRUG LABEL: MediAc
								
NDC: 68647-111 | Form: TABLET
Manufacturer: Feelgood Health
Category: homeopathic | Type: HUMAN OTC DRUG LABEL
Date: 20100714

ACTIVE INGREDIENTS: CAUSTICUM 30 [hp_C]/1 1; CALCIUM SULFIDE 30 [hp_C]/1 1; ACTIVATED CHARCOAL 30 [hp_C]/1 1; SILICON DIOXIDE 6 [hp_C]/1 1
INACTIVE INGREDIENTS: LACTOSE

MEDIAC

DESCRIPTION

Treats symptoms of acne vulgaris including blackheads and pustules

INDICATIONS AND USAGE

Indications: Homeopathic remedy for blemished skin, pustules and pimples.

DOSAGE AND ADMINISTRATION

Dosage: Dissolve 2 tablets in a clean mouth 3 times daily (may be increased to 5 times daily). May be used together with ClearSkin-A Gel™ and ClearSkin Skin Wash™ for complete skin care.

GENERAL PRECAUTIONS

Caution: If symptoms persist or worsen, a health care professional should be consulted. Keep this and all medicines from the reach of children.

ACTIVE INGREDIENT

Ingredients: Each dose contains equal parts of Causticum (30C) (HPUS), Hepar sulph calc (30C) (HPUS), Carbo veg (30C) (HPUS), Silicea (6C) (HPUS)

Lactose (inactive ingredient).

PREGNANCY

If pregnant or breastfeeding, ask a health professional before use.

USER SAFETY WARNINGS

Contains no gluten, artificial flavors, colors or preservatives. Safe for all ages and during pregnancy.

PATIENT COUNSELING INFORMATION

All Native Remedies health products are especially formulated by experts in the field of natural health and are manufactured according to the highest pharmaceutical standards for maximum safety and effectiveness. For more information, visit us at www.nativeremedies.com

Distributed by

Native Remedies, LLC

6531 Park of Commerce Blvd.

Suite 160

Boca Raton, FL 33487

Phone: 1.877.289.1235

International: + 1.561.999.8857

The letters HPUS indicate that the component(s) in this product is (are) officially monographed in the Homeopathic Pharmacopoeia of the United States.